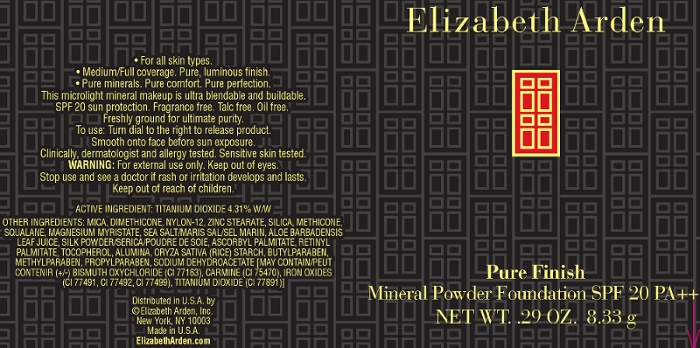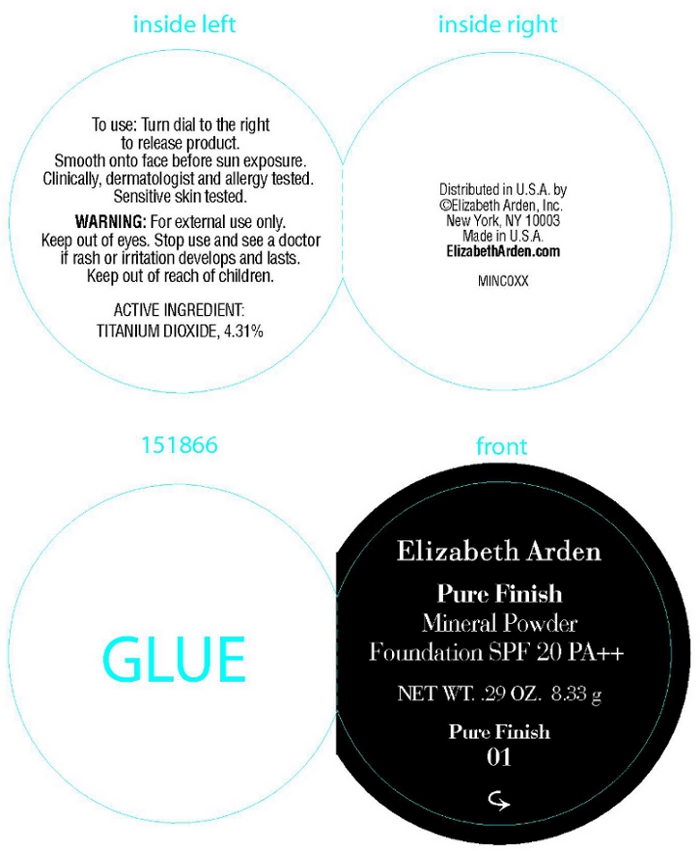 DRUG LABEL: Pure Finish Mineral Powder Foundation SPF 20 Pure Finish 8
NDC: 67938-1397 | Form: POWDER
Manufacturer: Elizabeth Arden, Inc
Category: otc | Type: HUMAN OTC DRUG LABEL
Date: 20110111

ACTIVE INGREDIENTS: TITANIUM DIOXIDE 0.358 g/8.33 g
INACTIVE INGREDIENTS: MICA; DIMETHICONE; ZINC STEARATE; SILICON DIOXIDE; SQUALANE; MAGNESIUM MYRISTATE; SEA SALT; STARCH, RICE; ALUMINUM OXIDE; METHYLPARABEN; SODIUM DEHYDROACETATE; ALOE VERA LEAF; PROPYLPARABEN; VITAMIN A PALMITATE; ASCORBYL PALMITATE; BUTYLPARABEN; ALPHA-TOCOPHEROL

BP1397

DESCRIPTION

For all skin types. Mediun/full coverage. Pure, luminous finish. Pure minerals. Pure comfort. Pure perfection. This microlight mineral makeup is ultra blendable and buildable. SPF 20 sun protection. Fragrance free. Talc free. Oil free. Freshly ground for ultimate purity. Clinically and dermatologist tested. Sensititve skin tested.

INDICATIONS AND USAGE

To Use: Turn dial to the right to release product. Smooth on to face before sun exposure.

WARNINGS

WARNING: For extrenal use only. Keep out of eyes. Stop use and see a doctor if rash or irritation develops and lasts.

OTC - ACTIVE INGREDIENT

Active Ingredient: Titanium Dioxide 4.31% w/w.

INACTIVE INGREDIENT

Other Ingredients: Mica, Dimethicon, Nylon-12, Zinc Stearate, Silica, Methicon, Squalane, Magnesium Myristate, Sea Salt/Maris Sal/Sel Marin, Aloe Barbadensis Leaf Jucie, Silk Powder/Serica/Poudre de Soice, Ascorbyl Palmitate, Retinyl Palmitate, Tocopherol, Alumina, Oryza Sative (Rice) Starch, Butylparaben, Methylparaben, Propylparaben, Sodium Dehydroacetate. [May Contain/Peut Contenir (+/-) Bismuth Oxychloride (CI 77163), Carmine (CI 75470), Iron Oxides (CI 77491, CI 77492, CI 77499), Titanium Dioxide (CI 77891).]

DOSAGE & ADMINISTRATION

Smooth on to face.

OTC - KEEP OUT OF REACH OF CHILDREN

Keep out of reach of children.

OTC - PURPOSE

Provides SPF 20 sun protection.

OTC - WHEN USING

Keep out of eyes.